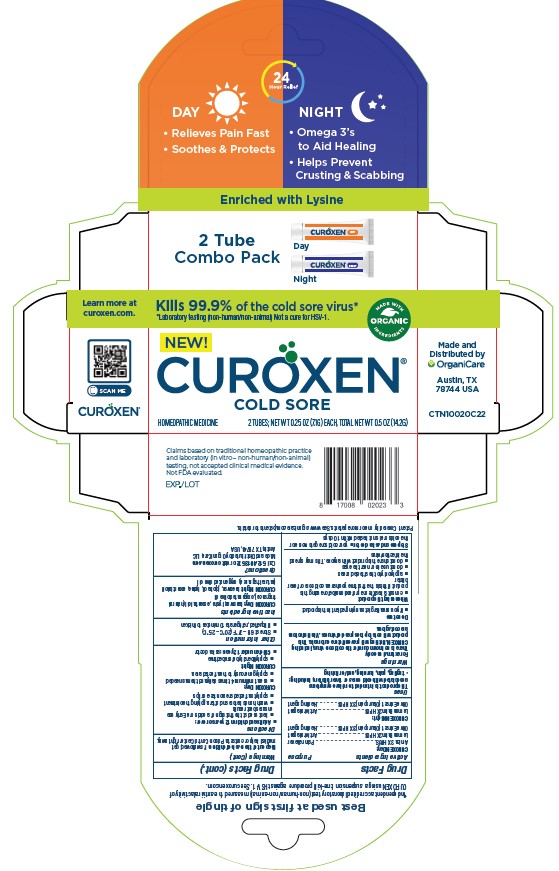 DRUG LABEL: Curoxen Cold Sore Day
NDC: 71042-014 | Form: OINTMENT
Manufacturer: OrganiCare Nature's Science, LLC
Category: homeopathic | Type: HUMAN OTC DRUG LABEL
Date: 20241212

ACTIVE INGREDIENTS: LEMON BALM OIL 1 g/100 g; ARNICA MONTANA 0.1 g/100 g
INACTIVE INGREDIENTS: OLIVE OIL 94.8 g/100 g; VETIVER OIL 2 g/100 g

Curoxen Cold Sore Day and Night

Active Ingredients

Active ingredients Purpose
CUROXEN Day:
Arnica 3X HPUS..............................................Pain reliever
Lemon Balm 2X HPUS ....................................Antiviral agent
Olive Extract (Oleuropein) 3X HPUS ...............Healing agent
CUROXEN Night:
Lemon Balm 2X HPUS ....................................Antiviral agent
Olive Extract (Oleuropein) 3X HPUS ...............Healing agent

Ask a doctor

Stop use and ask a doctor  your cold sore gets worse or
the cold sore is not healed within 10 days

Do Not Use

 if you are allergic to any ingredient in this product

Keep out of the reach of children. If swallowed, get
medical help or contact a Poison Control Center right away.

Uses

This product is intended to relieve symptoms
associated with cold sores or fever blisters, including:
· tingling, pain, burning, and/or itching

Questions

Call 512.401.3572 or visit curoxen.com
Made and Distributed by OrganiCare, LLC
Austin, TX 78744, USA

Stop use and ask a doctor  your cold sore gets worse or
the cold sore is not healed within 10 days

Directions

 Adults and children 12 years or over:
 best used at the first sign of a cold sore. Early use
ensures best results
 wash hands before and after applying the ointment
 apply to affected area on face or lips
CUROXEN Day:
 use at minimum 4 times daily and then as needed
 apply generously to the affected area
CUROXEN Night:
 apply liberally before bedtime
 Children under 12 years: ask a doctor

When Using this Product

 consult a healthcare professional before using this
product if this is the first time you have a cold sore or fever
blister
 apply only to the affected areas
 do not use in or near the eyes
 do not share this product with anyone. This may spread
the infection/virus

Inactive Ingredients

CUROXEN Day: beeswax, lysine, essential oil (natural
fragrance), oxygenated olive oil
CUROXEN Night: beeswax, jojoba oil, lysine, essential oil
(natural fragrance), oxygenated olive oil

Other Information

 Store at 68 – 77° F (20° C – 25° C)
 If liquefied, refrigerate 10 minutes to thicken

Warnings

For external use only
There is no known cure for the cold sore virus, including
CUROXEN. Nothing will prevent future outbreaks. This
product will not stop the spread of viruses. Viral infections
are contagious.